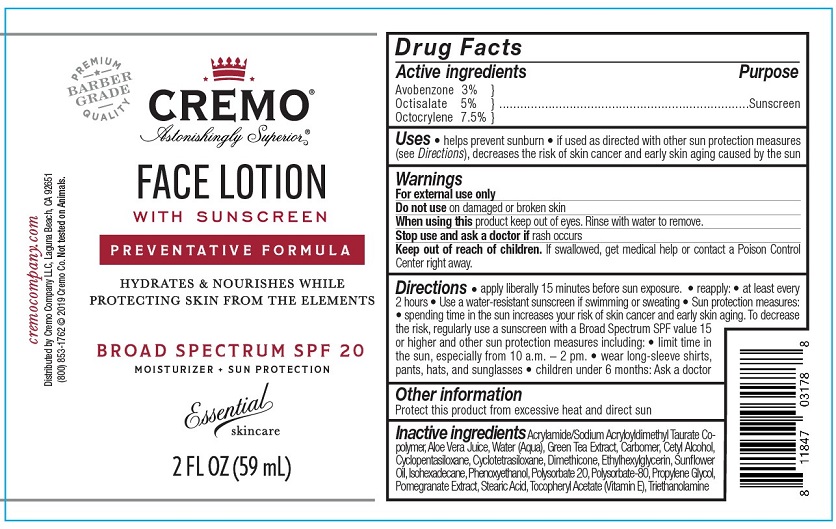 DRUG LABEL: Cremo Sunscreen
NDC: 71825-102 | Form: LOTION
Manufacturer: Cremo company
Category: otc | Type: HUMAN OTC DRUG LABEL
Date: 20191209

ACTIVE INGREDIENTS: AVOBENZONE 3 g/100 mL; OCTISALATE 5 g/100 mL; OCTOCRYLENE 7.5 g/100 mL
INACTIVE INGREDIENTS: CETYL ALCOHOL; GREEN TEA LEAF; WATER; SODIUM ACRYLOYLDIMETHYLTAURATE-ACRYLAMIDE COPOLYMER (1:1; 90000-150000 MPA.S); CYCLOMETHICONE 5; ALOE VERA LEAF; PROPYLENE GLYCOL; ETHYLHEXYLGLYCERIN; DIMETHICONE; ISOHEXADECANE; CYCLOMETHICONE 4; PHENOXYETHANOL; POLYSORBATE 20; POLYSORBATE 80; STEARIC ACID; ALPHA-TOCOPHEROL ACETATE; POMEGRANATE; SUNFLOWER OIL; TROLAMINE; CARBOMER 940

Face Lotion with Sunscreen SPF 20

Drug Facts

Active ingredients

Avobenzone 3%

Octisalate 5%

Octocrylene 7.5%

Purpose

Sunscreen

Uses

- helps prevent sunburn
- if used as directed with other sun protection measures (see Directions) decreases the risk of skin cancer and early skin aging caused by the sun

Warnings

For external use only

Do not use on broken or damaged skin

When using this product keep out of eyes. Rinse with water to remove.

Stop use and ask a doctor if rash occurs

Keep out of reach of children. If swallowed, get medical help or contact a Poison Control Center right away.

Directions

- apply liberally 15 minutes before sun exposure
- reapply:
- at least every 2 hours
- use a water-resistant sunscreen if swimming or sweating
- Sun Protections Measures.
- spending time in the sun increases your risk of skin cancer and early skin aging. To decrease this risk, regularly use a sunscreen with a Broad Spectrum SPF value of 15 or higher and other sun protection measures including:
- limit time in the sun, especially from 10 a.m. - 2 p.m.
- wear long-sleeve shirts, pants, hats, and sunglasses
- children under 6 months: Ask a doctor

Other information

Protect this product from excessive heat and direct sun

INACTIVE INGREDIENT

Inactive ingredients Acrylamide/Sodium Acroylyldimethyl Taurate Copolymer, Aloe Vera Juice, Water (Aqua),Green Tea Extract, Carbomer, Cetyl Alcohol, Cyclopentasiloxane, Cyclotetrasiloxane, Dimethicone, Ethylhexylglycerin, Sunflower Oil, Isohexadecane, Phenoxyethanol, Polysorbate 20, Polysorbate-80, Propylene Glycol, Pomegranate Extract, Stearic Acid, Tocopheryl Acetate (Vitamin E), Triethanolamine

cremocompany.com

Distributed by Cremo Company LLC, Laguna Beach, CA 92651

(800) 853-1762 © 2019 Cremo Co. Not tested on Animals.

PACKAGE LABEL

Cremo®

Astonishingly Superior®

FACE LOTION WITH SUNSCREEN

PREVENTATIVE FORMULA

HYDRATES & NOURISHES WHILE PROTECTING SKIN FROM THE ELEMENTS

BROAD SPECTRUM SPF 20

MOISTURIZER + SUN PROTECTION

Essential skincare

2 FL OZ (59 mL)